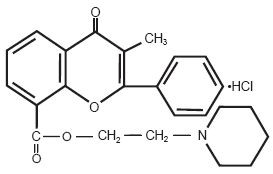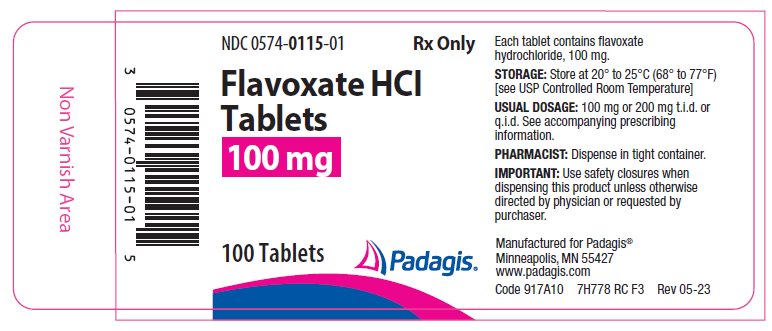 DRUG LABEL: FLAVOXATE HYDROCHLORIDE
NDC: 0574-0115 | Form: TABLET, FILM COATED
Manufacturer: Padagis US LLC
Category: prescription | Type: HUMAN PRESCRIPTION DRUG LABEL
Date: 20230531

ACTIVE INGREDIENTS: FLAVOXATE HYDROCHLORIDE 100 mg/1 1
INACTIVE INGREDIENTS: SILICON DIOXIDE; ETHYL ACRYLATE; HYPROMELLOSE, UNSPECIFIED; LACTOSE MONOHYDRATE; MAGNESIUM STEARATE; METHYL METHACRYLATE; MICROCRYSTALLINE CELLULOSE; NONOXYNOL-100; SODIUM STARCH GLYCOLATE TYPE A POTATO; HYPROMELLOSE 2910 (6 MPA.S); POLYETHYLENE GLYCOL, UNSPECIFIED

Flavoxate HCl Tablets
100 mg

PRESCRIBING INFORMATION

DESCRIPTION

Flavoxate HCl tablets contain flavoxate hydrochloride, a synthetic urinary tract spasmolytic.

Chemically, flavoxate hydrochloride is 2-piperidinoethyl 3-methyl-4-oxo-2-phenyl-4H-1-benzopyran-8-carboxylate hydrochloride. The empirical formula of flavoxate hydrochloride is C24H25NO4•HCl. The molecular weight is 427.94. The structural formula appears below:

Flavoxate HCl is supplied in tablets for oral administration. Each round, white, film-coated Flavoxate HCl tablet is debossed "PAD" and "0115" on one side and plain on the other side and contains flavoxate hydrochloride, 100 mg. Inactive ingredients consist of colloidal silicon dioxide, ethyl acrylate, hypromellose, lactose monohydrate, magnesium stearate, methyl methacrylate, microcrystalline cellulose, nonoxynol 100 and sodium starch glycolate. Film coating is composed of hypromellose 2910 6cP and polyethylene glycol.

CLINICAL PHARMACOLOGY

Flavoxate hydrochloride counteracts smooth muscle spasm of the urinary tract and exerts its effect directly on the muscle.

In a single study of 11 normal male subjects, the time to onset of action was 55 minutes. The peak effect was observed at 112 minutes. 57% of the flavoxate HCl was excreted in the urine within 24 hours.

INDICATIONS AND USAGE

Flavoxate HCl tablets are indicated for symptomatic relief of dysuria, urgency, nocturia, suprapubic pain, frequency and incontinence as may occur in cystitis, prostatitis, urethritis, urethrocystitis/urethrotrigonitis. Flavoxate HCl tablets are not indicated for definitive treatment, but are compatible with drugs used for the treatment of urinary tract infections.

CONTRAINDICATIONS

Flavoxate HCl tablets are contraindicated in patients who have any of the following obstructive conditions: pyloric or duodenal obstruction, obstructive intestinal lesions or ileus, achalasia, gastrointestinal hemorrhage and obstructive uropathies of the lower urinary tract.

WARNINGS

Flavoxate HCl should be given cautiously in patients with suspected glaucoma.

PRECAUTIONS

Information for Patients:

Patients should be informed that if drowsiness and blurred vision occur, they should not operate a motor vehicle or machinery or participate in activities where alertness is required.

Carcinogenesis, Mutagenesis, Impairment of Fertility:

Mutagenicity studies and long-term studies in animals to determine the carcinogenic potential of flavoxate HCl have not been performed.

Pregnancy:

Teratogenic Effects-Pregnancy Category B.

Reproduction studies have been performed in rats and rabbits at doses up to 34 times the human dose and revealed no evidence of impaired fertility or harm to the fetus due to flavoxate HCl. There are, however, no well-controlled studies in pregnant women. Because animal reproduction studies are not always predictive of human response, this drug should be used during pregnancy only if clearly needed.

Nursing Mothers:

It is not known whether this drug is excreted in human milk. Because many drugs are excreted in human milk, caution should be exercised when flavoxate HCl is administered to a nursing woman.

Pediatric Use:

Safety and effectiveness in children below the age of 12 years have not been established.

ADVERSE REACTIONS

The following adverse reactions have been observed, but there are not enough data to support an estimate of their frequency.

Gastrointestinal: Nausea, vomiting, dry mouth.

CNS: Vertigo, headache, mental confusion, especially in the elderly, drowsiness, nervousness.

Hematologic: Leukopenia (one case which was reversible upon discontinuation of the drug).

Cardiovascular: Tachycardia and palpitation.

Allergic: Urticaria and other dermatoses, eosinophilia and hyperpyrexia.

Ophthalmic: Increased ocular tension, blurred vision, disturbance in eye accommodation.

Renal: Dysuria.

OVERDOSAGE

The oral LD50 for flavoxate HCl in rats is 4273 mg/kg. The oral LD50 for flavoxate HCl in mice is 1837 mg/kg.

It is not known whether flavoxate HCl is dialyzable.

DOSAGE AND ADMINISTRATION

Adults and children over 12 years of age:

One or two 100 mg tablets 3 or 4 times a day. With improvement of symptoms, the dose may be reduced. This drug cannot be recommended for infants and children under 12 years of age because safety and efficacy have not been demonstrated in this age group.

HOW SUPPLIED

Flavoxate HCl Tablets, 100 mg, are supplied as round, white, film-coated tablets debossed "PAD" and "0115" on one side and plain on the other side, in bottles of 100.

100 mg 100's:
NDC 0574-0115-01

Store at 20° to 25°C (68° to 77°F) [see USP Controlled Room Temperature]

Manufactured For
Padagis®
Minneapolis, MN 55427
www.padagis.com

Rev 05-23
7H700 RC PH3
Code 917A00

PRINCIPAL DISPLAY PANEL - 100 mg Tablet Bottle

NDC 0574-0115-01

Rx Only

Flavoxate HCl Tablets

100 mg

100 Tablets